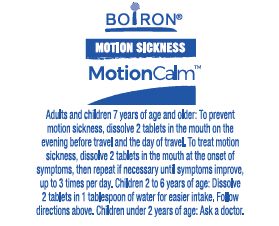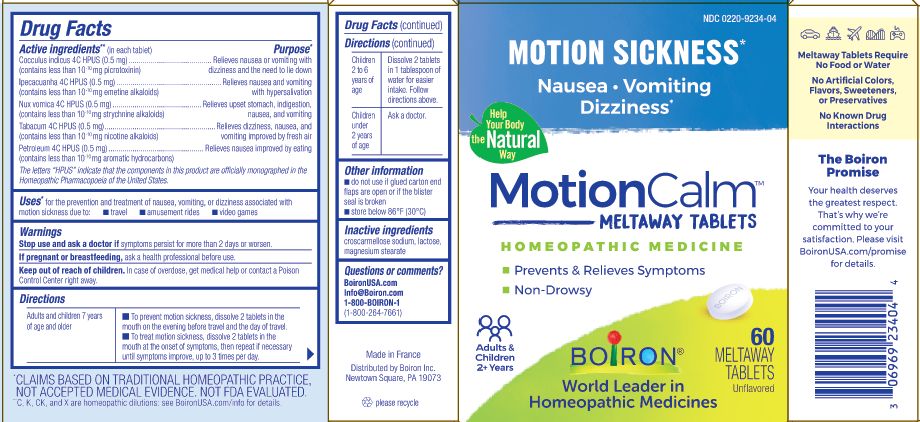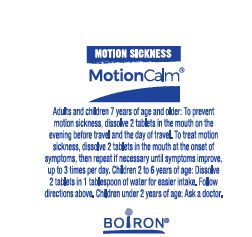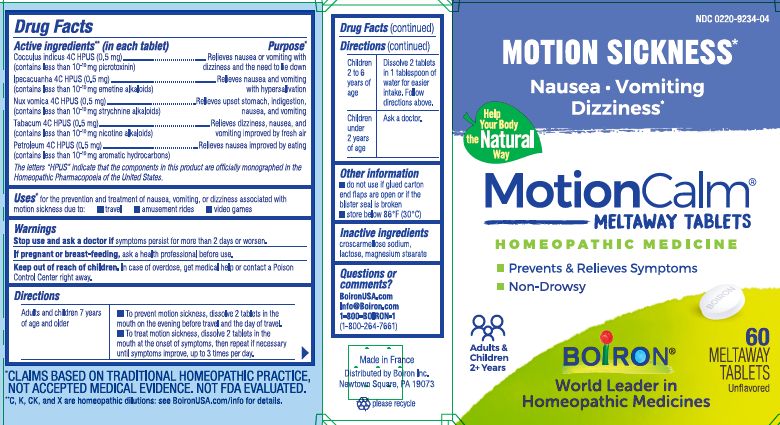 DRUG LABEL: MotionCalm
NDC: 0220-9234 | Form: TABLET
Manufacturer: Boiron
Category: homeopathic | Type: HUMAN OTC DRUG LABEL
Date: 20230530

ACTIVE INGREDIENTS: IPECAC 4 [hp_C]/1 1; STRYCHNOS NUX-VOMICA SEED 4 [hp_C]/1 1; KEROSENE 4 [hp_C]/1 1; ANAMIRTA COCCULUS SEED 4 [hp_C]/1 1; TOBACCO LEAF 4 [hp_C]/1 1
INACTIVE INGREDIENTS: CROSCARMELLOSE SODIUM; MAGNESIUM STEARATE; LACTOSE, UNSPECIFIED FORM

MotionCalm

Active ingredients** (in each tablet)

Cocculus indicus 4C HPUS (0.5 mg) (contains less than 10-10 mg picrotoxinin)

Ipecacuanha 4C HPUS (0.5 mg) (contains less than 10-10 mg emetine alkaloids)

Nux vomica 4C HPUS (0.5 mg) (contains less than 10-10 mg strychnine alkaloids)

Tabacum 4C HPUS (0.5 mg) (contains less than 10-10 mg nicotine alkaloids)

Petroleum 4C HPUS (0.5 mg) (contains less than 10-10 mg aromatic hydrocarbons)

The letters "HPUS" indicate that the components in this product are officially monographed in the Homeopathic Pharmacopoeia of the United States.

Purpose*

Cocculus indicus 4C HPUS Relieves nausea or vomiting with dizziness and the need to lie down

Ipecacuanha 4C HPUS Relieves nausea and vomiting with hypersalivation

Nux vomica 4C HPUS Relieves upset stomach, indigestion, nausea, and vomiting

Tabacum 4C HPUS Relieves dizziness, nausea, and vomiting improved by fresh air

Petroleum 4C HPUS Relieves nausea improved by eating

Uses*

for the prevention and treatment of nausea, vomiting, or dizziness associated with motion sickness due to: travel, amusement rides, video games

Stop use and ask a doctor if symptoms persist for more than 2 days or worsen.

PREGNANCY OR BREAST FEEDING

If pregnant or breastfeeding, ask a health professional before use.

Keep out of reach of children. In case of overdose, get medical help or contact a Poison Control Center right away.

Directions

Adults and children 7 years of age and older

- To prevent motion sickness, dissolve 2 tablets in the mouth on the evening before travel and day of travel.
- To treat motion sickness, dissolve 2 tablets in the mouth at the onset of symptoms, then repeat if necessary until symptoms improve, up to 3 times per day.

Children 2 to 6 years of age

- Dissolve 2 tablets in 1 tablespoon of water for easier intake. Follow directions above.

Children under 2 years of age

- Ask a doctor.

INACTIVE INGREDIENT

croscarmellose sodium, lactose, magnesium stearate

do not use if glued carton end flaps are open or if the blister seal is broken.

store below 86°F (30°C)

60 meltaway tablets unflavored

Motion Sickness*

Nausea Vomiting Dizziness*

Prevents & Relieves Symptoms

Non-Drowsy

*CLAIMS BASED ON TRADITIONAL HOMEOPATHIC PRACTICE, NOT ACCEPTED MEDICAL EVIDENCE. NOT FDA EVALUATED.

**C,K,CK, and X are homeopathic dilutions: see BoironUSA.com/info for details.

QUESTIONS

BoironUSA.com

info@Boiron.com

1-800-BOIRON-1

(1-800-264-7661)

Made in France

Distributed by Boiron, Inc.

Newtown Square, PA 19073